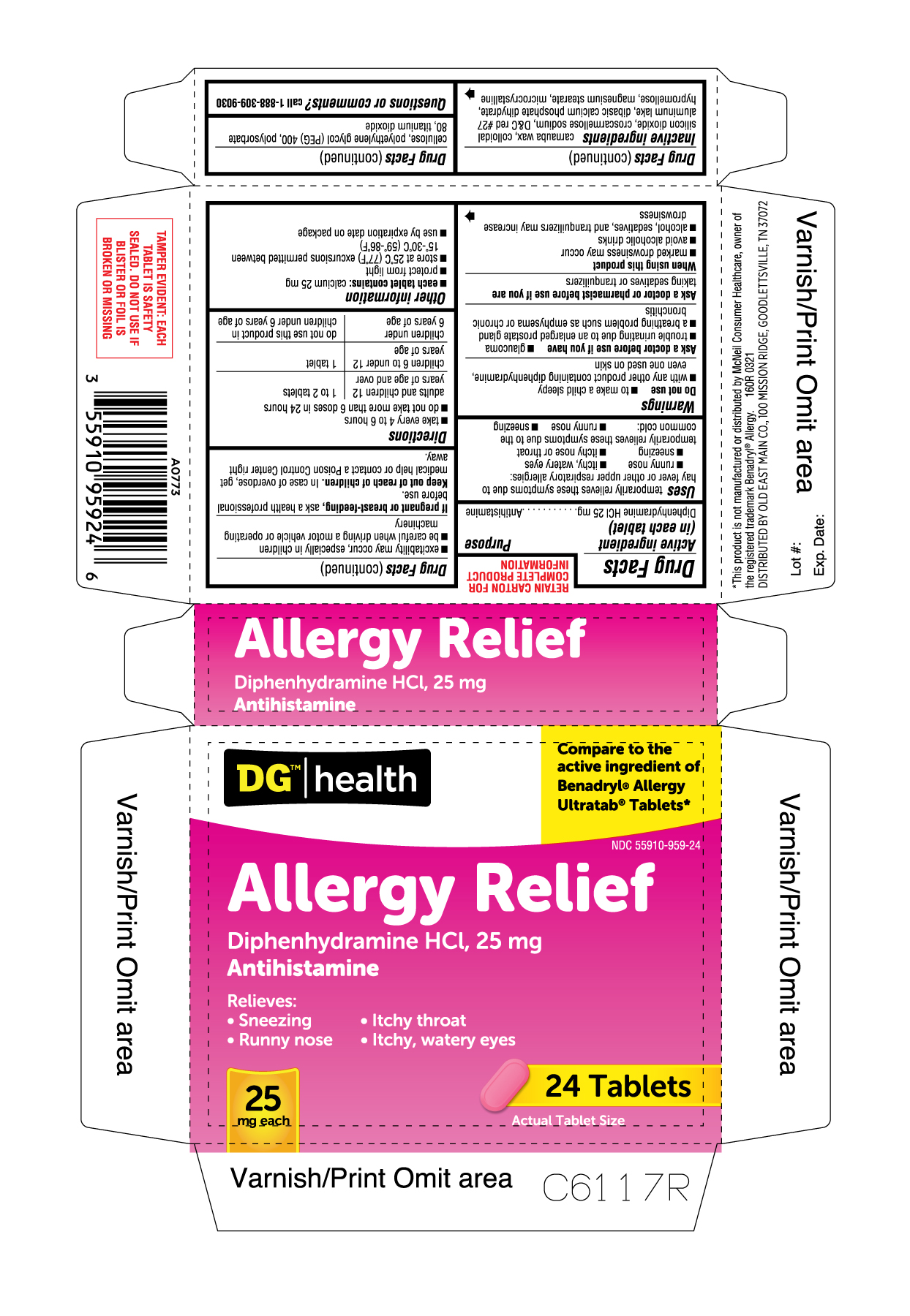 DRUG LABEL: Allergy Relief
NDC: 55910-959 | Form: TABLET, FILM COATED
Manufacturer: DOLGENCORP, LLC
Category: otc | Type: HUMAN OTC DRUG LABEL
Date: 20250210

ACTIVE INGREDIENTS: DIPHENHYDRAMINE HYDROCHLORIDE 25 mg/1 1
INACTIVE INGREDIENTS: CARNAUBA WAX; SILICON DIOXIDE; DIBASIC CALCIUM PHOSPHATE DIHYDRATE; HYPROMELLOSES; TITANIUM DIOXIDE; MICROCRYSTALLINE CELLULOSE; MAGNESIUM STEARATE; POLYETHYLENE GLYCOL 400; CROSCARMELLOSE SODIUM; D&C RED NO. 27 ALUMINUM LAKE; POLYSORBATE 80

160R 55910 959 Dollar General DIPHENHYDRAMINE HYDROCHLORIDE 24CT

Active Ingredient (in each tablet)

Diphenhydramine Hydrochloride 25mg

Purpose

Antihistamine

INDICATIONS AND USAGE

Uses temporarily relieves these symptoms due to hay fever or other upper respiratory allergies:

- runny nose
- sneezing
- itchy, watery eyes
- itchy nose or throat

temporarily relieves these symptoms due to the common cold:

- runny nose
- sneezing

Warnings
Do not use

- to make a child sleepy
- with any other product containing diphenhydramine, even one used on skin

Ask a doctor before use if you have

- glaucoma
- trouble urinating due to an enlarged prostate gland
- a breathing problem such as emphysema or chronic bronchitis

Ask a doctor or pharmacist before use if you are taking sedatives or tranquilizers

When using this product

- marked drowsiness may occur
- avoid alcoholic drinks
- alcohol, sedatives, and tranquilizers may increase drowsiness
- excitability may occur, especially in children
- be careful when driving a motor vehicle or operating machinery

PREGNANCY OR BREAST FEEDING

If pregnant or breast-feeding, ask a health professional before use.

Keep out of reach of children. In case of overdose, get medical help or contact a Poison Control Center right away.

Directions

- take every 4 to 6 hours
- do not take more than 6 doses in 24 hours

adults and children 12 years of age and over: 1 to 2 tablets
children 6 to under 12 years of age: 1 tablet
children under 6 years of age: do not use this product in children under 6 years of age

OTHER INFORMATION

- each tablet contains: calcium 25 mg
- protect from light
- store at 25°C (77°F) excursions permitted between 15°-30°C (59°-86°F)
- use by expiration date on package

INACTIVE INGREDIENT

Inactive ingredients carnauba wax, colloidal silicon dioxide, croscarmellose sodium, D&C Red #27 Aluminum Lake, dibasic calcium phosphate dihydrate, hypromellose, magnesium stearate, microcrystalline cellulose, polyethylene glycol (PEG) 400, polysorbate 80, titanium dioxide

Questions or Comments? call 1-888-309-9030